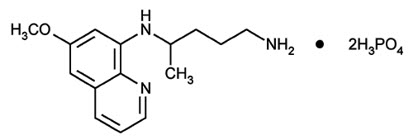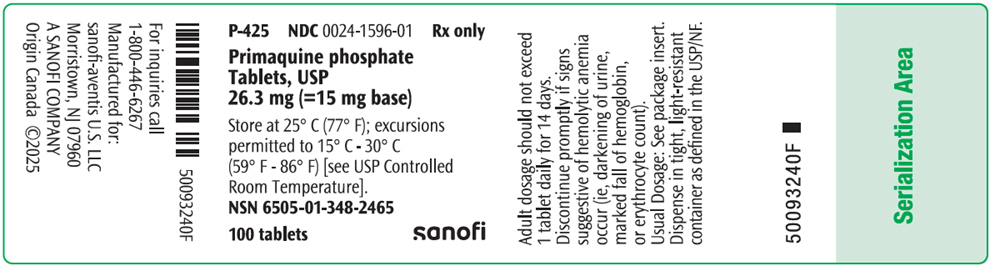 DRUG LABEL: Primaquine Phosphate
NDC: 0024-1596 | Form: TABLET, FILM COATED
Manufacturer: Sanofi-Aventis U.S. LLC
Category: prescription | Type: HUMAN PRESCRIPTION DRUG LABEL
Date: 20260211

ACTIVE INGREDIENTS: PRIMAQUINE PHOSPHATE 15 mg/1 1
INACTIVE INGREDIENTS: CARNAUBA WAX; LACTOSE, UNSPECIFIED FORM; MAGNESIUM STEARATE; MICROCRYSTALLINE CELLULOSE; POLYETHYLENE GLYCOL 400; POLYSORBATE 80; FERRIC OXIDE RED; TALC; TITANIUM DIOXIDE; HYPROMELLOSE 2910 (15000 MPA.S); STARCH, CORN

PRIMAQUINE PHOSPHATE TABLETS, USP

DESCRIPTION

Primaquine phosphate is 8-[(4-amino-1-methylbutyl) amino]-6-methoxyquinoline phosphate, a synthetic compound with potent antimalarial activity. The molecular formula of Primaquine phosphate is C15H21N3O∙2H3PO4 and its molecular weight is 455.34. The structural formula of Primaquine phosphate is:

Figure 1: Primaquine phosphate structure.

Each Primaquine phosphate tablet contains 26.3 mg of primaquine phosphate (equivalent to 15 mg of primaquine base). The dosage is customarily expressed in terms of the base.

Inactive Ingredients: Carnauba Wax, Hydroxypropyl Methylcellulose, Lactose, Magnesium Stearate, Microcrystalline Cellulose, Polyethylene Glycol 400, Polysorbate 80, Pregelatinized Starch, Red Ferric Oxide, Talc, Titanium Dioxide.

CLINICAL PHARMACOLOGY

Microbiology

Mechanism of Action

Primaquine phosphate is an 8-aminoquinoline antimalarial drug. The mechanism of action has not been fully established. The major assumptions are an inhibition of the mitochondrial system of dormant parasites, and an oxidative stress generated through reactive metabolites in infected cells. In humans, primaquine phosphate activity is probably related to hydroxylated metabolites generated intrahepatically by CYP2D6.

Antimicrobial Activity

Primaquine phosphate is active against the dormant liver forms of P.vivax, namely hypnozoites, as well as exoerythrocytic stages of the parasite. Thereby, it prevents the development of the blood (erythrocytic) forms of the parasite which are responsible for relapses in vivax malaria. Primaquine phosphate is also active against gametocytes of Plasmodium falciparum.

Resistance

Development of resistance to primaquine phosphate in Plasmodium species has not been well studied.

Pharmacokinetics

Following single oral dosing, the Cmax and AUC of primaquine increase approximately dose-proportionally over a primaquine base dose range of 15 mg to 45 mg (3 times the approved dose).

The pharmacokinetic parameters and properties of primaquine and carboxyprimaquine (main circulating metabolite not expected to be active) in patients with P. vivax malaria following Oral Administration of Primaquine phosphate Tablets are provided in TABLE 1.

TABLE 1: Summary of Pharmacokinetic Parameters and Properties (Mean ± SD) in Patients with P. vivax malaria.
PK Parameter [15 mg once daily in adult patients (18 years of age and older) with P. vivax malaria, unless otherwise specified] | Day | Primaquine |  | Carboxyprimaquine
Cmax (ng/mL) | 1 | 50.7 ± 21.2 |  | 291 ± 52
Cmax (ng/mL) | 14 | 49.7 ± 14.4 |  | 432 ±112
AUC or AUC0–24 (µg/mL*h) [AUC for primaquine, AUC0–24 for carboxyprimaquine] | 1 | 0.48 ± 0.26 |  | 5.15 ± 1.01
AUC or AUC0–24 (µg/mL*h) | 14 | 0.49 ± 0.19 |  | 7.24 ± 1.82
Primaquine
Absorption
Bioavailability [Healthy participants] |  |  | >70 %
Tmax |  |  | 2.3 ± 1.1 hours
Effect of food on Primaquine Phosphate Tablet (relative to fasting) [Values refer to increase in mean systemic exposure with bread and butter: 82% fat, ~28g fat after single dose of 30 mg Primaquine in healthy participants] Geometric mean [95% confidence interval] |  |  | ↑ 14% [3, 27] (AUC); ↑ 26% [12, 40] (Cmax)
Distribution
% Bound to human plasma proteins |  |  | 74% (mainly to alpha 1 acid glycoprotein)
Volume of distribution (V) [IV dose administration of [^14C]-primaquine in healthy participants] |  |  | 243 ± 69 L
Metabolism
Metabolic pathways |  |  | -Oxidative deamination, MAO-A -Hydroxylation of the quinoline ring, CYP2D6 -Direct conjugations
Elimination
Major route of elimination |  |  | Metabolism
Apparent Clearance (CL/F) |  |  | 37.6 ± 14.7 L/hr
Mean terminal half-life (t1/2) [The mean terminal half-life of carboxyprimaquine is approximately 22 hours] |  |  | 5.6 ± 1.0 hours
% of dose excreted in urine [Oral administration of [^14C]-primaquine in healthy participants; no data in feces] , [The main circulating metabolite, carboxyprimaquine is subjected to further metabolism and not eliminated through urine] |  |  | 64%, (including 3.6% of primaquine, the remnant being metabolites other than carboxyprimaquine)
Cmax=maximum plasma concentration; AUC=area under the plasma concentration-time curve from time zero up to infinity; MAO-A = monoamine oxidase A

Specific Populations

Gender and ethnicity

No gender nor ethnicity effect has been evidenced in studies conducted to date.

Elderly patients

There are no pharmacokinetics studies in patients older than 52 years of age.

Hepatic impairment

Single dose pharmacokinetics study performed in patients with mild or moderate hepatic impairment indicate that only moderate hepatic dysfunction impacted significantly the PK of primaquine with a 3-fold lower primaquine Cmax in patients with moderate hepatic dysfunction as compared to healthy subjects. The primaquine AUC was not significantly modified.

No data are available after repeated dosing in patients with hepatic impairment. It is not known whether in patients with hepatic impairment, accumulation of primaquine and its metabolites could occur or if there could be an impact on generation of metabolites contributing to pharmacological activity.

Renal impairment

Single dose pharmacokinetics studies performed in patients with chronic severe (eGFR 15 to 29 mL/min) or end-stage (< 15 mL/min) renal impairment indicate higher primaquine Cmax (up to 1.7-fold higher as compared to healthy subjects) but no evidence of major difference in AUC or t1/2. It is not known whether after repeated dosing there could be an accumulation of metabolites that are mainly excreted by renal route.

Drug Interaction Studies

Effect of other Drugs on the Pharmacokinetics of primaquine

In vitro data suggest primaquine is not a substrate of either P-gp or BCRP membrane transporters.

Effect of primaquine on the Pharmacokinetics of other drugs

In vitro data suggest primaquine has the potential to inhibit CYP1A2 enzyme activity, but no or low potential to inhibit MAO-A, MAO-B, or CYP450 isoforms 2A6, 2C8, 2C9, 2C19, 2D6, 3A4 enzymes involved in drug biotransformation.

In vitro data suggest primaquine has the potential to inhibit the P-gp membrane transporter.

Pharmacogenomics

Published clinical reports indicate that primaquine is a CYP2D6 substrate. Experiments in mice indicate primaquine activity likely depends on the formation of CYP2D6 metabolite(s). CYP2D6 has variants that affect CYP2D6 metabolic function. CYP2D6 poor metabolizers are individuals with two nonfunctional alleles (e.g., CYP2D6*5/*5), and as a result have no CYP2D6 activity. CYP2D6 intermediate metabolizers are individuals with a combination of nonfunctional, reduced, or normal function alleles, and as a result have reduced CYP2D6 activity (e.g., CYP2D6*1/*5, CYP2D6*4/*10).

Individuals who are CYP2D6 intermediate or poor metabolizers exhibit a prolonged primaquine half-life and increased primaquine plasma concentrations when compared to individuals who are CYP2D6 normal metabolizers. CYP2D6 metabolizer status may be associated with variability in clinical response to Primaquine phosphate Tablets (see PRECAUTIONS).

INDICATIONS AND USAGE

Primaquine phosphate Tablets are indicated for the radical cure (prevention of relapse) of vivax malaria.

CONTRAINDICATIONS

Known hypersensitivity reactions to primaquine phosphate, other 8- aminoquinolones, or to any component in Primaquine phosphate Tablets.

Severe glucose-6-phosphate dehydrogenase (G6PD) deficiency (see WARNINGS, Hemolytic Anemia).

Pregnant women (see WARNINGS, Pregnancy).

Breastfeeding by a lactating woman when the infant is found to be G6PD deficient or if G6PD status is unknown (see WARNINGS, Nursing Mothers).

Because quinacrine hydrochloride appears to potentiate the toxicity of antimalarial compounds which are structurally related to primaquine, the use of quinacrine in patients receiving Primaquine phosphate Tablets is contraindicated. Similarly, Primaquine phosphate Tablets should not be administered to patients who have received quinacrine recently, as toxicity is increased.

WARNINGS

Hemolytic Anemia

Hemolytic reactions (moderate to severe) may occur in individuals with G6PD deficiency and in individuals with a family or personal history of favism. Areas of high prevalence of G6PD deficiency are Africa, Southern Europe, Mediterranean region, Middle East, South-East Asia, and Oceania. People from these regions have a greater tendency to develop hemolytic anemia due to a congenital deficiency of erythrocytic G6PD while receiving primaquine and related drugs.

Due to the risk of hemolytic anemia in patients with G6PD deficiency, G6PD testing must be performed before using primaquine. Before initiating treatment, obtain baseline hemoglobin and hematocrit. In case of severe anemia, postpone the G6PD test and decision on treatment with primaquine until recovery.

Due to the limitations of G6PD tests, physicians need to be aware of residual risk of hemolysis and adequate medical support and follow-up to manage hemolytic risk should be available. This is of particular importance in individuals with a personal or family history of hemolytic anemia.

Patients with G6PD Deficiency

Primaquine phosphate Tablets are contraindicated in patients with severe G6PD deficiency (see CONTRAINDICATIONS).

In case of mild to moderate G6PD deficiency, a decision to prescribe primaquine must be based on an assessment of the risks and benefits of using primaquine. If primaquine administration is considered, baseline hematocrit and hemoglobin must be checked before treatment and close hematological monitoring (e.g., at day 3 and 8) is required. Adequate medical support to manage hemolytic risk should be available.

Patients with Unknown G6PD Status

When the G6PD status is unknown and G6PD testing is not available, a decision to prescribe primaquine must be based on an assessment of the risks and benefits of using primaquine. Risk factors for G6PD deficiency or favism must be assessed. Baseline hematocrit and hemoglobin must be checked before treatment and close hematological monitoring (e.g., at day 3 and 8) is required. Adequate medical support to manage hemolytic risk should be available.

Patients without G6PD Deficiency

In G6PD normal patients it is also advisable to perform routine blood examinations (particularly blood cell counts and hemoglobin determinations) during therapy.

Risk of Hemolysis with Other Drugs

Avoid the concurrent administration of hemolytic agents in all patients (see CLINICAL PHARMACOLOGY, Drug Interactions). Warn patients to discontinue the use of Primaquine phosphate Tablets promptly if signs suggestive of hemolytic anemia occur (such as darkening of the urine, pale skin, shortness of breath, dizziness, and fatigue) and to contact their healthcare professional immediately.

Pregnancy

Safe usage of Primaquine phosphate Tablets in pregnancy has not been established. Primaquine is contraindicated in pregnant women. The use of Primaquine phosphate Tablets during pregnancy may cause hemolytic anemia in a G6PD-deficient fetus. Even if a pregnant woman has normal levels of G6PD, the fetus could be G6PD-deficient (see CONTRAINDICATIONS). Animal data show toxicity to reproduction and embryofetal development. (See PRECAUTIONS, Animal Pharmacology and/or Animal Toxicology).

Nonclinical data from studies conducted in bacteria and in animals treated with primaquine show evidence of gene mutations and chromosomal/DNA damage, teratogenicity, and injury to embryos and developing fetuses when primaquine is administered to pregnant animals. Inform patients of the potential for adverse genetic and reproductive effects associated with primaquine treatment (see PRECAUTIONS, Carcinogenesis, Mutagenesis, and Impairment of Fertility, and Animal Pharmacology and/or Animal Toxicology).

Use in Females and Males of Reproductive Potential

Pregnancy Testing

Sexually active females of reproductive potential should have a pregnancy test prior to starting treatment with primaquine.

Contraception

Patients should avoid pregnancy during treatment. Advise sexually active females of childbearing potential to use effective contraception (methods that result in less than 1% pregnancy rates) when using primaquine and for 6 months after stopping treatment). Advise treated males whose partners may become pregnant, to use a condom while on treatment and for 3 months after stopping treatment with primaquine.

Nursing Mothers

A breastfed infant with G6PD deficiency is at risk for hemolytic anemia from exposure to primaquine. Infant G6PD status should be checked before breastfeeding begins. Primaquine phosphate Tablets are contraindicated in breastfeeding women when the infant is found to be G6PD deficient or the G6PD status of the infant is unknown (see CONTRAINDICATIONS). Advise the woman with a G6PD-deficient infant or if the G6PD status of the infant is unknown not to breastfeed.

The presence of primaquine and its major metabolite in breast milk and infant plasma were evaluated in a published study of 21 G6PD-normal lactating women and their G6PD-normal infants aged 28 days or older. After repeat administration of a 0.5 mg/kg/day primaquine base dose for 14 days in the lactating women, low concentrations of primaquine and carboxyprimaquine were measured both in breast milk and in infant plasma. The estimated infant ingested dose was found to be less than 1% of a 0.5 mg/kg/day primaquine base dose determined from an observed milk to maternal plasma AUC ratio of 0.34 (range: 0.12 to 0.64) and assuming an infant milk consumption of 150 mL/kg/day. Infant primaquine concentrations in plasma were below measurement thresholds (2.28 ng/mL) in all but 1 infant capillary plasma sample (2.6 ng/mL), and carboxyprimaquine concentrations in plasma were likewise unmeasurable in the majority of infant samples (range, 4.88 ng/mL [measurement threshold] to maximum value 25.8 ng/mL). There is no information on the effects of Primaquine phosphate Tablets on the breastfed infant, or the effects on milk production.

PRECAUTIONS

Methemoglobinemia

Primaquine may cause a transient increase in methemoglobin levels up to 10% in patients without risk factors (see ADVERSE REACTIONS). Methemoglobinemia may be severe in patients who are deficient in nicotinamide adenine dinucleotide (NADH), methemoglobin reductase or treated with methemoglobinemia-inducing drugs such as dapsone or sulfonamide, (see PRECAUTIONS, Drug Interactions). Monitor methemoglobin levels closely in these cases.

Advise all patients to seek immediate medical attention if signs of methemoglobinemia occur such as bluish lips or nails.

Leukopenia

Primaquine may cause leukopenia in patients with established granulocytopenia, such as rheumatoid arthritis and lupus erythematosus. Avoid concurrent administration of bone-marrow depressants.

Discontinue the use of primaquine promptly if there is a sudden decrease in leukocyte count.

Potential Prolongation of QT Interval

Due to potential for QT interval prolongation, monitor ECG when using primaquine in patients with cardiac disease, long QT syndrome, a history of ventricular arrhythmias, uncorrected hypokalemia and/or hypomagnesemia, or bradycardia (<50 bpm), and during concomitant administration with QT interval prolonging agents (see PRECAUTIONS, Drug Interactions, ADVERSE REACTIONS, and OVERDOSAGE).

Strong CYP2D6 Inhibitors, CYP2D6 Poor or Intermediate Metabolizers, and Treatment Failure

Based on published non-clinical reports, primaquine activity likely depends on the formation of CYP2D6 metabolite(s). Therefore, CYP2D6 genetic variation or drugs that impact CYP2D6 activity may be associated with variability in clinical response to Primaquine phosphate Tablets.

Limited published clinical data reported higher treatment failure rates in patients who were CYP2D6 poor or intermediate metabolizers than in patients who were CYP2D6 normal metabolizers (see CLINICAL PHARMACOLOGY).

When possible, consider alternative medications that are not strong CYP2D6 inhibitors. Increase monitoring for possible relapse in patients with concurrent strong CYP2D6 inhibitor usage or in patients who are CYP2D6 poor or intermediate metabolizers (see PRECAUTIONS, Drug Interactions).

In case of treatment failure, after checking patient's compliance to treatment, reassess use of CYP2D6 inhibitors and assess the patient's CYP2D6 metabolizer status, if feasible. For patients who are CYP2D6 poor or intermediate metabolizers, alternative treatment should be considered.

Carcinogenesis, Mutagenesis, Impairment of Fertility

No carcinogenicity studies have been conducted with primaquine. No fertility studies have been conducted with primaquine. Primaquine is reported in the literature to be a weak genotoxic agent which elicits both gene mutations^1, chromosomal damage and DNA strand breaks^2. The publications reported positive results in the in vitro reverse gene mutation assays using bacteria (Ames test) ^3,4 and in the in vivo studies using rodents (mouse bone marrow cell sister chromatid exchange, mouse bone marrow cell chromosome abnormality, and rat DNA strand breaks in multiple organs) ^(2, 5). The genotoxicity data obtained in vitro and in rodent models are suggestive of a human risk for genotoxicity with primaquine administration (see WARNINGS, Usage in Pregnancy).

Animal Pharmacology and/or Animal Toxicology

Literature data on reproductive toxicology identified embryo-fetal development toxicity. In studies in rats, teratogenic effects on fetus were observed (see WARNINGS, Usage in Pregnancy).

In the first reproductive toxicity study^6, primaquine was administered orally to rats between gestation day (GD) 6 and GD15 at dose levels of 10.3, 30.8 and 61.5 mg/kg/day (as base) (representing approximatively 7, 20 and 40 times the human dose [HD] on a body surface area comparison) when considering a human body weight of 60 kg). High dose levels induced death of pregnant females in almost all cases, while lower dose levels caused maternal toxicity. At cesarean section, embryo resorption, a decrease in fetal survival rate and body size, internal abnormalities (including hydrocephalia, heterotaxia), and an increase in skeletal variations were observed at the mid dose-level. There were no fetal abnormalities at the low dose level providing a potential safety margin of at least 7 times the recommended clinical dose.

For the second reproductive toxicity study^7, 6 to10 animals per group were used. Dose levels of 0.57, 5.7, 11.4 and 34 mg/kg/day of primaquine (as base) (representing approximatively 0.4, 4, 7 and 22 times the HD on a body surface area comparison) were administered orally to Sprague Dawley rats between GD8 and GD16, or of 57 mg/kg only once on GD13 (representing more than 37 times the HD on a body surface area comparison). A total of 1/7 and 4/6 pregnant females at 34 mg/kg/day and at 57 mg/kg, respectively, died. Primaquine-associated teratogenic malformations (including cleft palate and small chin) were observed in 4/54 fetuses in the 57 mg/kg single-dose group.

Drug Interactions

Pharmacodynamics Interactions

Quinacrine

Concurrent use of quinacrine (mepacrine) and Primaquine phosphate Tablets are contraindicated. Increased toxicity was seen when quinacrine was used with pamaquine, another 8-aminoquinoline (see CONTRAINDICATIONS).

Hemolytic Agents and Methemoglobinemia-Inducing Drugs

The concurrent administration of hemolytic agents or methemoglobinemia-inducing drugs and primaquine should be avoided (see PRECAUTIONS). If the concurrent administration cannot be avoided, close blood monitoring is required.

QT Interval Prolonging Drugs

The pharmacodynamic interaction potential to prolong the QT interval of the electrocardiogram between Primaquine phosphate Tablets and other drugs that effect cardiac conduction is unknown. If Primaquine phosphate Tablets are used concomitantly with other drugs that prolong the QT interval, close and frequent electrocardiogram monitoring is advised (see PRECAUTIONS, ADVERSE REACTIONS, and OVERDOSAGE).

Effects of Other Drugs on the Pharmacokinetics of Primaquine

Strong CYP2D6 Inhibitors

Published clinical and non-clinical reports indicate reduced CYP2D6 activity may decrease the formation of active metabolites of primaquine, which may reduce antimalarial efficacy of Primaquine phosphate Tablets (see CLINICAL PHARMACOLOGY, Pharmacogenomics). Where possible, consider alternative medications that are not strong CYP2D6 inhibitors. If concurrent use with Primaquine phosphate Tablets is necessary, increase monitoring for possible relapse.

Concomitant use of an MAO-A inhibitor in patients with reduced or absent CYP2D6 activity (e.g., strong CYP2D6 inhibitor, CYP2D6 intermediate or poor metabolizer) is expected to increase primaquine exposure which may increase the risk of adverse reactions (see CLINICAL PHARMACOLOGY, Pharmacogenomics). Defer initiation of MAO-A inhibitor therapy or consider alternative drug therapy in patients with reduced or absent CYP2D6 activity until primaquine treatment is completed. If concurrent use with Primaquine phosphate Tablets is necessary, increase patient monitoring for potential adverse reactions (see PRECAUTIONS).

Effects of Primaquine on the Pharmacokinetics of Other Drugs

CYP1A2 Substrates

Published clinical and non-clinical reports indicate primaquine inhibits CYP1A2 enzyme activity and thus may lead to increased exposure of CYP1A2 substrate drugs (e.g., duloxetine, alosetron, theophylline and tizanidine) when co-administered with Primaquine phosphate Tablets. Since data are limited, no predictions can be made regarding the extent of the impact on CYP1A2 substrate drug exposures. Increase monitoring for adverse reactions associated with the CYP1A2 substrate drug when concurrently administered with Primaquine phosphate tablets.

CYP3A4 Substrates

Refer to the Prescribing Information for a CYP3A substrate where minimal concentration changes may lead to serious adverse reactions (e.g. rivaroxaban, calcineurin inhibitors, ergot derivatives, tyrosine kinase inhibitors) for the recommended dosage modification and/or monitoring.

Published clinical reports indicate primaquine may inhibit CYP3A4 enzyme activity and thus may lead to increased exposure of oral CYP3A4 substrate drugs when co-administered with Primaquine phosphate Tablets. Since data are limited, no predictions can be made regarding the extent of the impact on oral CYP3A4 substrate drug exposures. Increase monitoring for adverse reactions associated with CYP3A4 substrate drugs that prolong the QT interval (e.g., pimozide) or where minimal concentration changes may lead to serious adverse reactions when concurrently administered with Primaquine phosphate Tablets.

P-gp Substrates

Refer to the Prescribing Information for a P-gp substrate where minimal concentration changes may lead to serious adverse reactions (e.g., digoxin and dabigatran) for the recommended dosage modification and/or monitoring.

In vitro observations suggest that primaquine inhibits the P-gp membrane transporter. Therefore, there is a potential for increased concentrations of drugs that are P-gp substrates when co-administered with Primaquine phosphate Tablets. Increase monitoring for adverse reactions associated with P-gp substrate drugs where minimal concentration changes may lead to serious adverse reactions when concomitantly administered with Primaquine phosphate Tablets.

Pediatric Use

Safety and effectiveness in pediatric patients have not been established.

Primaquine phosphate Tablets are contraindicated in breastfeeding women when the infant is found to be G6PD deficient or the G6PD status of the infant is unknown (see CONTRAINDICATIONS and WARNINGS, Nursing Mothers).

Geriatric Use

Clinical studies of Primaquine phosphate Tablets did not include sufficient numbers of subjects aged 65 and over to determine whether they respond differently from younger subjects. Other reported clinical experience has not identified differences in responses between the elderly and younger patients.

In general, dose selection for an elderly patient should be cautious, usually starting at the low end of the dosing range, reflecting the greater frequency of decreased hepatic, renal, or cardiac function, and of concomitant disease or other drug therapy.

Hepatic Impairment

Efficacy and safety of Primaquine phosphate Tablets after repeated dosing have not been assessed in patients with hepatic impairment. Primaquine is metabolized in the liver to generate active metabolites, and it is not known if efficacy could be affected in patients with hepatic impairment. Because of limited data, there is no specific dosing adjustment. If Primaquine phosphate Tablets are administered to such patients, monitoring of efficacy and for primaquine-related adverse reactions is needed, in particular in patients with severe hepatic impairment (see CLINICAL PHARMACOLOGY).

Renal Impairment

The efficacy and safety of Primaquine phosphate Tablets after repeated dosing have not been assessed in patients with renal impairment. Because of limited data, there is no specific dosing adjustment. If Primaquine phosphate Tablets are administered to such patients, monitoring of efficacy and for primaquine-related adverse reactions is needed, in particular in patients with severe renal impairment (see CLINICAL PHARMACOLOGY).

ADVERSE REACTIONS

Gastrointestinal: Nausea, vomiting, epigastric distress, abdominal cramps.

Hematologic: Leukopenia, hemolytic anemia, decreased hemoglobin, methemoglobinemia.

Hemolytic anemia occurs commonly in patients with G6PD deficiency and may be severe or fatal in patients with severe G6PD deficiency (see WARNINGS).

Methemoglobin levels are usually <10%, but methemoglobinemia may be severe in nicotinamide adenine dinucleotide (NADH) methemoglobin reductase deficient individuals or in patients with other risk factors (see PRECAUTIONS).

Leukopenia was observed in patients with rheumatoid arthritis or lupus erythematosus (see PRECAUTIONS).

Cardiac: Cardiac arrhythmia and QT interval prolongation (see PRECAUTIONS, OVERDOSAGE).

Nervous System: Dizziness.

Skin and Soft Tissue: Rash, pruritus.

OVERDOSAGE

Signs and symptoms

Symptoms of overdosage of primaquine phosphate include abdominal cramps, vomiting, burning epigastric distress, central nervous system disturbances including headache, insomnia, and cardiovascular disturbances, including cardiac arrhythmia and QT interval prolongation, methemoglobinemia (indicated by cyanosis), moderate leukocytosis or leukopenia, granulocytopenia, and anemia. Acute hemolysis may occur with particular severity in G6PD deficient patients.

Management

Treatment of overdosage consists of institution of appropriate symptomatic and/or supportive therapy. Consider contacting a poison center or a medical toxicologist for overdosage management recommendations.

DOSAGE AND ADMINISTRATION

Primaquine phosphate Tablets are recommended only for the radical cure of vivax malaria, the prevention of relapse in vivax malaria, or following the termination of chloroquine phosphate suppressive therapy in an area where vivax malaria is endemic. Patients suffering from an attack of vivax malaria or having parasitized red blood cells should receive a course of chloroquine phosphate, which quickly destroys the erythrocytic parasites and terminates the paroxysm. Primaquine phosphate Tablets should be administered concurrently to eradicate the exoerythrocytic parasites in adults at a dosage of 1 tablet (equivalent to 15 mg base) daily for 14 days.

Primaquine phosphate Tablets can be taken with or without food. Administration of Primaquine phosphate Tablets with food may reduce the incidence of gastrointestinal symptoms.

HOW SUPPLIED

Primaquine phosphate Tablets are supplied as pink, convex, discoid, film-coated tablets of 26.3 mg (= 15 mg base), printed with a "W" and "P97" on one side.

Available in bottles of 100 tablets. (NDC 0024-1596-01)

STORAGE AND HANDLING

Store at 25° C (77° F); excursions permitted to 15° C – 30° C (59° F – 86° F) [see USP Controlled Room Temperature]

Dispense in tight, light-resistant container as defined in the USP/NF.

CLINICAL STUDIES

Persons with acute attacks of vivax malaria, provoked by the release of erythrocytic forms of the parasite, respond readily to therapy, particularly to chloroquine phosphate. Primaquine eliminates tissue (exoerythrocytic) infection and prevents relapses in experimentally induced vivax malaria in human volunteers and in persons with naturally occurring infections and is a valuable adjunct to conventional therapy in vivax malaria.

REFERENCES

1. Shubber EK, Jacobson-Kram D, Williams JR. Comparison of the Ames assay and the induction of sister chromatid exchanges: results with ten pharmaceuticals and five selected agents. Cell Biol Toxicol. 1986;2:379–99.
2. Chatterjee T, Muhkopadhyay A, Khan KA, Giri AK. Comparative mutagenic and genotoxic effects of three antimalarial drugs, chloroquine, primaquine and amodiaquine. Mutagenesis. 1998;13:619–24.
3. Marss TC. Bright JE, Morris BC. Methemoglobinogenic potential of primaquine and its mutagenicity in the Ames test. Toxicol Lett. 1987;36:281–7.
4. Ono T, Norimatsu M, Yoshimura H. Mutagenic evaluation of primaquine, pentaquine and pamaquine in the Salmonella/mammalian microsome assay. Mutat Res. 1994;325:7–10.
5. Giovanella F, Ferreira GK, de Prá1 SDT, et al. Effects of primaquine and chloroquine on oxidative stress parameters in rats. An Acad Bras Cienc (Annals of the Brazilian Academy of Sciences). 2015;87:1487–1496.
6. Trutter JA, Reno FE, Durloo RS. Teratogenicity studies with a candidate antileishmanial drug. The Toxicologist. 1983;3:65.
7. Beveridge E, Caldwell IC, Latter VS, Neal RA, Udall V, Waldron MM. The activity against Trypanosoma cruzi and cutaneous leishmaniasis, and toxicity, of moxipraquine (349C59). Trans R Soc Trop Med Hyg. 1980;74:43–51.
8. Bennett JW, Pybus BS, Yadava A, Tosh D, Sousa JC, McCarthy WF, et al. Primaquine failure and cytochrome P-450 2D6 in Plasmodium vivax malaria. N Engl J Med.2013;369(14):1381–82

Rx Only

Revised February 2026

Manufactured for:
sanofi-aventis U.S. LLC
Morristown, NJ 07960
A SANOFI COMPANY
©2026 sanofi-aventis U.S. LLC

PRINCIPAL DISPLAY PANEL - 26.3 mg Tablet Bottle Label

P-425
NDC 0024-1596-01
Rx only

Primaquine phosphate
Tablets, USP
26.3 mg (=15 mg base)

Store at 25° C (77° F); excursions
permitted to 15° C - 30° C
(59° F - 86° F) [see USP Controlled
Room Temperature].
NSN 6505-01-348-2465

100 tablets
sanofi